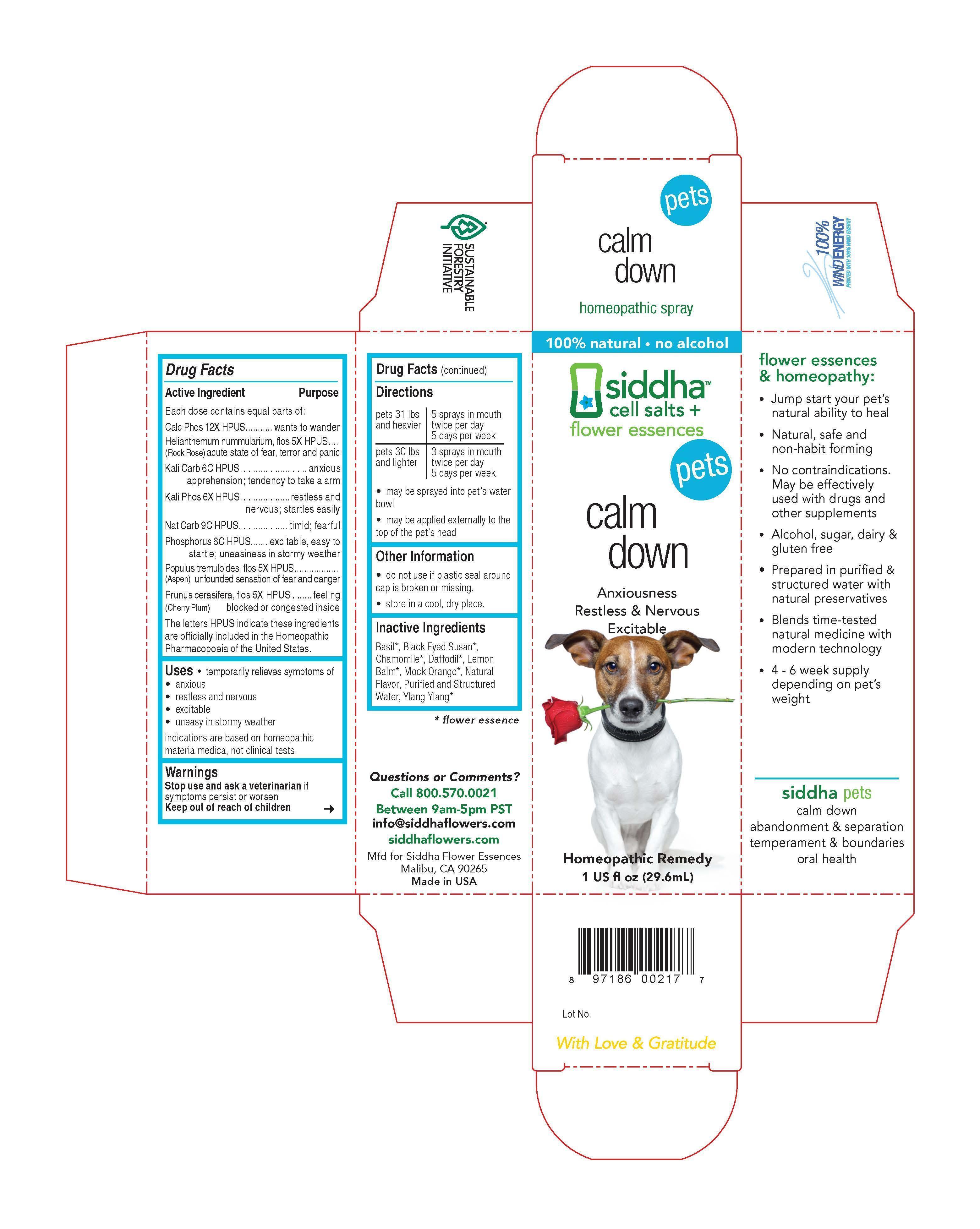 DRUG LABEL: calm down
NDC: 69779-022 | Form: SPRAY
Manufacturer: Siddha Flower Essences LLC
Category: homeopathic | Type: OTC ANIMAL DRUG LABEL
Date: 20150409

ACTIVE INGREDIENTS: TRIBASIC CALCIUM PHOSPHATE  12 [hp_X]/29.6 mL; HELIANTHEMUM NUMMULARIUM FLOWER 5 [hp_X]/29.6 mL; POTASSIUM CARBONATE 6 [hp_C]/29.6 mL; POTASSIUM PHOSPHATE, DIBASIC  6 [hp_X]/29.6 mL; SODIUM CARBONATE 9 [hp_C]/29.6 mL; PHOSPHORUS     6 [hp_C]/29.6 mL; POPULUS TREMULA FLOWERING TOP  5 [hp_X]/29.6 mL; PRUNUS CERASIFERA FLOWER 5 [hp_X]/29.6 mL
INACTIVE INGREDIENTS: OCIMUM BASILICUM FLOWERING TOP; MATRICARIA RECUTITA FLOWERING TOP; NARCISSUS PSEUDONARCISSUS FLOWER ; MELISSA OFFICINALIS FLOWERING TOP ; WATER; CANANGA ODORATA FLOWER

Drug Facts

Active Ingredient

Each dose contains equal parts of:

Calc Phos 12X HPUS
Helianthemum nummularium, flos (Rock Rose) 5X HPUS
Kali Carb 6C HPUS
Kali Phos 6X HPUS
Nat Carb 9C HPUS
Phosphorus 6C HPUS
Populus tremuloides, flos (Aspen) 5X HPUS
Prunus cerasifera, flos (Cherry Plum) 5X HPUS

Purpose

Each dose contains equal parts of:
Calc Phos 12X HPUS............................................................wants to wander
Helianthemum nummularium, flos (Rock Rose) 5X HPUS.........acute state of fear, terror and panic
Kali Carb 6C HPUS...............................................................anxious apprehension; tendency to take alarm
Kali Phos 6X HPUS..............................................................restless and nervous; startles easily
Nat Carb 9C HPUS...............................................................timid; fearful
Phosphorus 6C HPUS...........................................................excitable, east to startle; uneasiness in stormy weather
Populus tremuloides, flos (Aspen) 5X HPUS...........................unfounded sensation of fear and danger
Prunus cerasifera, flos (Cherry Plum) 5X HPUS......................feeling blocked or congested inside
The letters HPUS indicate these ingredients are officially included in the Homeopathic Pharmacopoeia of the United States.

Uses

- temporarily relieves symptoms of
- anxious
- restless and nervous
- excitable
- uneasy in stormy weather

indications are based on homeopathic materia medica, not clinical tests.

Warnings

Stop use and ask a veterinarian if symptoms persist or worsen

Keep out of reach of children

Directions

pets 31 lbs and heavier | 5 sprays in mouth twice per day 5 days per week
pets 30 lbs and lighter | 3 sprays in mouth twice per day 5 days per week

- may be sprayed into pet's water bowl
- may be applied externally to the top of pet's head

Other Information

- do not use if plastic seal around cap is broken or missing.
- store in a cool, dry place.

Inactive Ingredients

Basil*, Black Eyed Susan*, Chamomile*, Daffodil*, Lemon Balm*, Mock Orange*, Natural Flavor, Purified and Structured Water, Ylang Ylang*

*flower essence

Questions or Comments?
Call 800.570.0021
Between 9am-5pm PST
info@siddhaflowers.com
siddhaflowers.com
Mfd for Siddha Flower Essences
Malibu, CA 90265
Made in USA

Side Panel

flower essences and homeopathy:

- Jump start your pet's natural ability to heal
- Natural, safe and non-habit forming
- No contraindications. May be effectively used with drugs and other supplements
- Alcohol, sugar, dairy and gluten free
- Prepared in purified and structured water with natural preservatives
- Blends time-tested natural medicine with modern technology
- 4 - 6 week supply depending on pet's weight

siddha pets
calm down
abandonment and separation
temperament and boundaries
oral health

Principal Display Panel

100% natural - no alcohol
siddha cell salts + flower essences
pets
calm down
Anxiousness
Restless and Nervous
Excitable
Homeopathic Remedy
1 US fl oz (29.6mL)